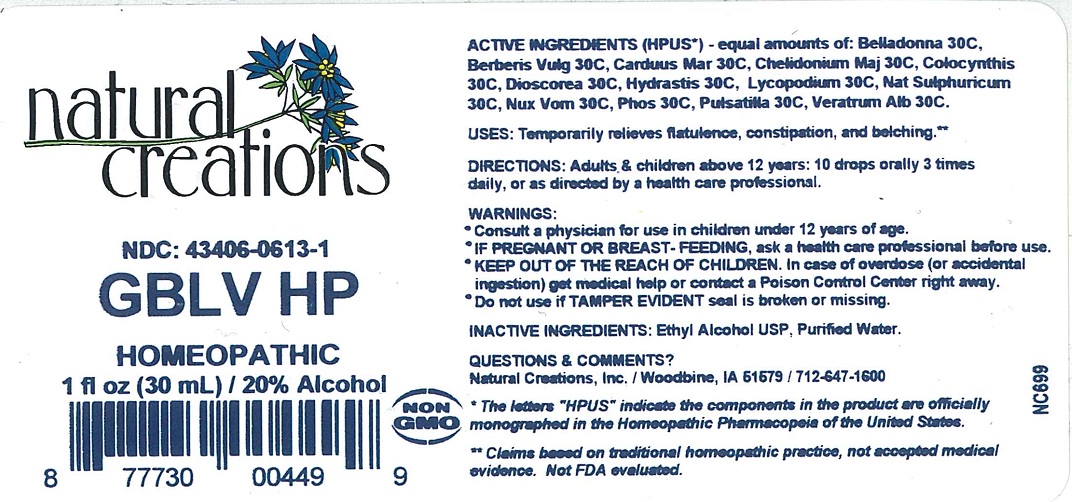 DRUG LABEL: GBLV HP
NDC: 43406-0613 | Form: LIQUID
Manufacturer: Natural Creations, Inc.
Category: homeopathic | Type: HUMAN OTC DRUG LABEL
Date: 20251212

ACTIVE INGREDIENTS: ATROPA BELLADONNA 30 [hp_C]/1 mL; BERBERIS VULGARIS ROOT BARK 30 [hp_C]/1 mL; MILK THISTLE 30 [hp_C]/1 mL; CHELIDONIUM MAJUS 30 [hp_C]/1 mL; CITRULLUS COLOCYNTHIS FRUIT PULP 30 [hp_C]/1 mL; DIOSCOREA VILLOSA TUBER 30 [hp_C]/1 mL; GOLDENSEAL 30 [hp_C]/1 mL; LYCOPODIUM CLAVATUM SPORE 30 [hp_C]/1 mL; SODIUM SULFATE 30 [hp_C]/1 mL; STRYCHNOS NUX-VOMICA SEED 30 [hp_C]/1 mL; PHOSPHORUS 30 [hp_C]/1 mL; ANEMONE PULSATILLA 30 [hp_C]/1 mL; VERATRUM ALBUM ROOT 30 [hp_C]/1 mL
INACTIVE INGREDIENTS: WATER; ALCOHOL

GBLV HP

ACTIVE INGREDIENT

ACTIVE INGREDIENTS (HPUS*) - equal amounts of: Belladonna 30C, Berberis Vulg 30C, Carduus Mar 30C, Chelidonium Maj 30C, Colocynthis 30C, Dioscorea 30C, Hydrastis 30C, Lycopodium 30C, Nat Sulphuricum 30C, Nux Vom 30C, Phos 30C, Pulsatilla 30C, Veratrum Alb 30C.

PURPOSE

USES: Temporarily relieves flatulence, constipation, and belching.**

INDICATIONS AND USAGE

USES: Temporarily relieves flatulence, constipation, and belching.**

DOSAGE AND ADMINISTRATION

DIRECTIONS: Adults & children above 12 years: 10 drops orally 3 times daily, or as directed by a health care professional.

KEEP OUT OF REACH OF CHILDREN

KEEP OUT OF THE REACH OF CHILDREN. In case of overdose (or accidental ingestion) get medical help or contact a Poison Control Center right away.

WARNINGS:

* Consult a physician for use in children under 12 years of age.

* IF PREGNANT OR BREAST-FEEDING, ask a health care professional before use.

* KEEP OUT OF THE REACH OF CHILDREN. In case of overdose (or accidental ingestion) get medical help or contact a Poison Control Center right away.

* Do not use if TAMPER EVIDENT seal is broken or missing.

INACTIVE INGREDIENTS: Ethyl Alcohol USP, Purified Water.

QUESTIONS & COMMENTS?

Natural Creations, Inc. / Woodbine, IA 51579 / 712-647-1600

REFERENCES

* The letters "HPUS" indicate the components in the product are officially monographed in the Homeopathic Pharmacopeia of the United States.

** These statements have not been reviewed by the FDA. They are based on traditional homeopathic practice.

LOT:

PACKAGE LABEL

NDC: 43406-0613-1

GBLV HP

Excess Bloating**

HOMEOPATHIC

1 fl oz (30 mL) / 20% Alcohol

GMP Logo UPC: 87773004499 NON GMO Logo